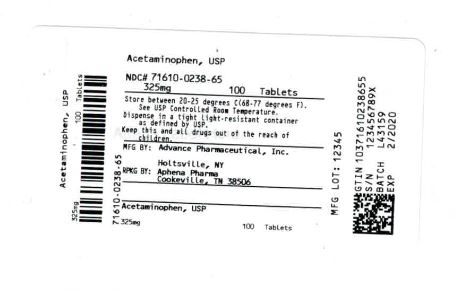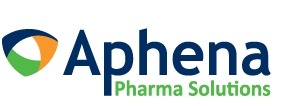 DRUG LABEL: Acetaminophen
NDC: 71610-238 | Form: TABLET
Manufacturer: Aphena Pharma Solutions - Tennessee, LLC
Category: otc | Type: HUMAN OTC DRUG LABEL
Date: 20190226

ACTIVE INGREDIENTS: ACETAMINOPHEN 325 mg/1 1
INACTIVE INGREDIENTS: POVIDONE; STARCH, CORN; SODIUM STARCH GLYCOLATE TYPE A POTATO; STEARIC ACID

ACETAMINOPHEN 325 mg

Active Ingredient

(in each tablet)

Acetaminophen 325 mg

Purpose

Pain Reliever / Fever Reducer

Uses

temporarily reduces fever and relieves minor aches and pains caused by

- common cold
- headache
- toothache
- backache
- muscular aches
- minor pain of arthritis
- premenstrual and menstrual cramps

Warnings

Liver warning: this product contains acetaminophen. Severe liver damage may occur if

- adult takes more than 12 tablets in 24 hours, which is the maximum daily amount
- child takes more than 5 tablets in 24 hours, which is the maximum daily amount
- taken with other drugs containing acetaminophen
- adult has 3 or more alcoholic drinks every day while using this product

do not use with any other drug containing acetaminophen (prescription or non prescription). If you are not sure whether a drug contains acetaminophen, ask a doctor or pharmacist.

Ask a doctor before use if the user has liver disease

Ask a doctor or pharmacist before use if the user is taking the blood thinning drug warfarin

Stop use and ask a doctor if

- adult’s pain gets worse or lasts more than 10 days
- child’s pain gets worse or lasts more than 5 days
- fever gets worse or lasts more than 3 days
- redness or swelling is present
- any new symptoms appear

If pregnant or breast-feeding, ask a health professional before use.

Overdose warning:Taking more than the recommended dose may cause liver damage. In case of overdose contact Poisom Control Center right away. Quick medical attention is critical for adults as well as children even if you do not notice any signs of symptoms.

Keep out of reach of children.

In case of overdose, get medical help or contact a Poison Control Center right away. Prompt medical attention is critical for adults as well as for children, even if you do not notice any signs or symptoms.

Directions

adults and children 12 years and over | 2 tablets every 4 to 6 hours while symptoms last, not more than 10 tablets in 24 hours. Do not use more than 10 days unless directed by doctor
children 6 to 11 years | 1 tablet every 4-6 hours while symptoms last, not more than 5 tablets in 24 hours. Do not use more than 5 days unless directed by doctor
children under 6 years | ask a doctor

Other Information

store at 15-30 °C (59-86 °F)

Inactive Ingredients

polyvinylpyrrolidone, pregelatinized corn starch, sodium starch glycolate, stearic acid

Questions or Comments

TAMPER EVIDENT: DO NOT USE IF IMPRINTED SAFETY SEAL UNDER CAP IS BROKEN OR MISSING

call 804-270-4498, 8.30 am-4.30 pm ET, Monday - Friday

Repackaging Information

Please reference the How Supplied section listed above for a description of individual tablets. This drug product has been received by Aphena Pharma - TN in a manufacturer or distributor packaged configuration and repackaged in full compliance with all applicable cGMP regulations. The package configurations available from Aphena are listed below:

Count | 325 mg
100 | 71610-238-65

Store between 20°-25°C (68°-77°F). See USP Controlled Room Temperature. Dispense in a tight light-resistant container as defined by USP. Keep this and all drugs out of the reach of children.

Repackaged by:
Cookeville, TN 38506
20190226JH

PRINCIPAL DISPLAY PANEL - 325 mg

NDC 71610-238 - Acetaminophen, USP 325 mg Tablets - Rx Only